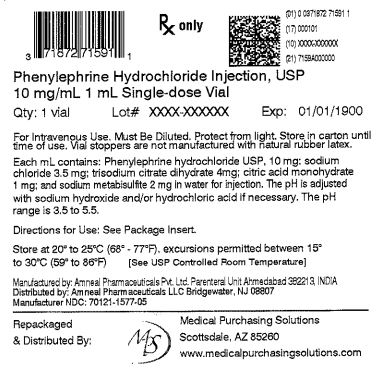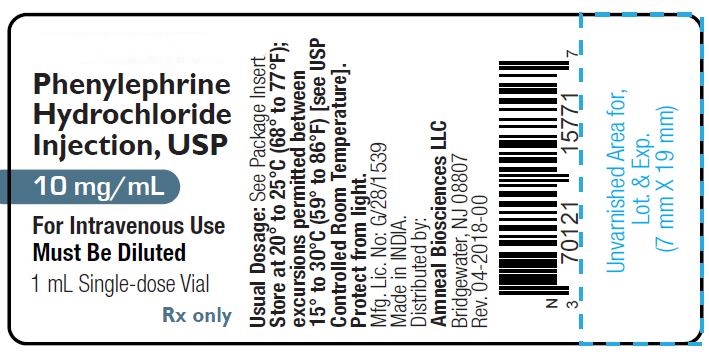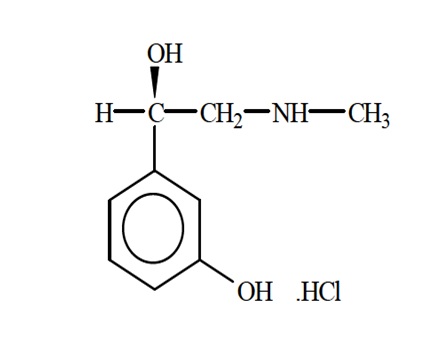 DRUG LABEL: Phenylephrine hydrochloride
NDC: 71872-7159 | Form: INJECTION
Manufacturer: Medical Purchasing Solutions, LLC
Category: prescription | Type: HUMAN PRESCRIPTION DRUG LABEL
Date: 20230515

ACTIVE INGREDIENTS: PHENYLEPHRINE HYDROCHLORIDE 10 mg/1 mL
INACTIVE INGREDIENTS: CITRIC ACID MONOHYDRATE 1 mg/1 mL; HYDROCHLORIC ACID; SODIUM CHLORIDE 3.5 mg/1 mL; SODIUM HYDROXIDE; SODIUM METABISULFITE 2 mg/1 mL; TRISODIUM CITRATE DIHYDRATE 4 mg/1 mL; WATER

HIGHLIGHTS OF PRESCRIBING INFORMATION

These highlights do not include all the information needed to use PHENYLEPHRINE HYDROCHLORIDE INJECTION safely and effectively. See full prescribing information for PHENYLEPHRINE HYDROCHLORIDE INJECTION.
PHENYLEPHRINE HYDROCHLORIDE injection for intravenous use
Initial U.S. Approval: 1954

1 INDICATIONS AND USAGE

Phenylephrine hydrochloride injection is an alpha-1 adrenergic receptor agonist indicated for the treatment of clinically important hypotension resulting primarily from vasodilation in the setting of anesthesia. (1)

2 DOSAGE AND ADMINISTRATION

Phenylephrine hydrochloride injection, 10 mg/mL, is injected intravenously either as a bolus or in a dilute solution as a continuous infusion.

Dilute before administration. (2)

Dosing for treatment of hypotension during anesthesia

- Bolus intravenous injection: 40 mcg to 100 mcg every 1 to 2 minutes as needed, not to exceed 200 mcg. (2)
- Intravenous infusion: 10 mcg/min to 35 mcg/min, titrating to effect, not to exceed 200 mcg/min. (2)

The dose should be adjusted according to the pressor response (i.e. titrate to effect). (2)

3 DOSAGE FORMS AND STRENGTHS

- Injection. (3)
- 1 mL single-dose vials containing 10 mg phenylephrine hydrochloride (10 mg/mL). (3)

4 CONTRAINDICATIONS

None. (4)

5 WARNINGS AND PRECAUTIONS

- Extravasation during intravenous administration may cause necrosis or sloughing of tissue. (5.3)
- Severe bradycardia and decreased cardiac output. (5.4)
- Allergic-type reactions: Sulfite. (5.5)
- Concomitant use with oxytocic drugs: Pressor effect of sympathomimetic pressor amines is potentiated. (5.8)

6 ADVERSE REACTIONS

Most common adverse reactions during treatment: nausea, vomiting, and headache. (6)

To report SUSPECTED ADVERSE REACTIONS, contact Amneal Biosciences at 1-855-266-3251 or FDA at 1-800-FDA-1088 or www.fda.gov/medwatch.

7 DRUG INTERACTIONS

- Agonistic effects with monoamine oxidase inhibitors (MAOI), oxytocin and oxytocic drugs, tricyclic antidepressants, angiotensin and aldosterone, atropine, steroids, norepinephrine transporter inhibitors, ergot alkaloids. (7.1)
- Antagonistic effects with α-adrenergic antagonists, phosphodiesterase Type 5 inhibitors, mixed α- and β-receptor antagonists, calcium channel blockers, benzodiazepines and ACE inhibitors, centrally acting sympatholytic agents. (7.2)

8 USE IN SPECIFIC POPULATIONS

- Pregnancy: Based on animal data, may cause fetal harm. (8.1)

FULL PRESCRIBING INFORMATION

1 INDICATIONS AND USAGE

Phenylephrine hydrochloride injection, 10 mg/mL is an alpha-1 adrenergic receptor agonist indicated for the treatment of clinically important hypotension resulting primarily from vasodilation in the setting of anesthesia.

2 DOSAGE AND ADMINISTRATION

2.1 General Dosage and Administration Instructions

Phenylephrine hydrochloride injection, 10 mg/mL must be diluted before administration as an intravenous bolus or continuous intravenous infusion to achieve the desired concentration:

- Bolus: Dilute with normal saline or 5% dextrose in water.
- Continuous infusion: Dilute with normal saline or 5% dextrose in water.

Parenteral drug products should be inspected visually for particulate matter and discoloration prior to administration. Do not use if the solution is colored or cloudy, or if it contains particulate matter. The diluted solution should not be held for more than 4 hours at room temperature or for more than 24 hours under refrigerated conditions. Discard any unused portion.

During phenylephrine hydrochloride injection administration:

- Correct intravascular volume depletion.
- Correct acidosis. Acidosis may reduce the effectiveness of phenylephrine.

2.2 Dosing for Treatment of Hypotension during Anesthesia

The following are the recommended dosages for the treatment of hypotension during anesthesia.

- The recommended initial dose is 40 to 100 mcg administered by intravenous bolus.
  May administer additional boluses every 1 to 2 minutes as needed; not to exceed a total dosage of 200 mcg.
- If blood pressure is below the target goal, start a continuous intravenous infusion with an infusion rate of 10 to 35 mcg/minute; not to exceed 200 mcg/minute.
- Adjust dosage according to the blood pressure goal.

2.3 Prepare a 100 mcg/mL Solution for Bolus Intravenous Administration

For bolus intravenous administration, prepare a solution containing a final concentration of 100 mcg/mL of phenylephrine hydrochloride injection:

- Withdraw 10 mg (1 mL of 10 mg/mL) of phenylephrine hydrochloride and dilute with 99 mL of 5% Dextrose Injection, USP or 0.9% Sodium Chloride Injection, USP.
- Withdraw an appropriate dose from the 100 mcg/mL solution prior to bolus intravenous administration.

2.4 Prepare a Solution for Continuous Intravenous Administration

For continuous intravenous infusion, prepare a solution containing a final concentration of 20 mcg/mL of phenylephrine hydrochloride in 5% Dextrose Injection, USP or 0.9% Sodium Chloride Injection, USP:

- Withdraw 10 mg (1 mL of 10 mg/mL) of phenylephrine hydrochloride and dilute with 500 mL of 5% Dextrose Injection, USP or 0.9% Sodium Chloride Injection, USP.

3 DOSAGE FORMS AND STRENGTHS

Phenylephrine hydrochloride injection, USP is a sterile, clear, colorless solution and supplied in 1 mL single-dose glass vials. Each mL contains phenylephrine hydrochloride USP, 10 mg.

4 CONTRAINDICATIONS

None

5 WARNINGS AND PRECAUTIONS

5.1 Exacerbation of Angina, Heart Failure, or Pulmonary Arterial Hypertension

Because of its increasing blood pressure effects, phenylephrine hydrochloride can precipitate angina in patients with severe arteriosclerosis or history of angina, exacerbate underlying heart failure, and increase pulmonary arterial pressure.

5.2 Peripheral and Visceral Ischemia

Phenylephrine hydrochloride can cause excessive peripheral and visceral vasoconstriction and ischemia to vital organs, particularly in patients with extensive peripheral vascular disease.

5.3 Skin and Subcutaneous Necrosis

Extravasation of phenylephrine hydrochloride can cause necrosis or sloughing of tissue. The infusion site should be checked for free flow. Care should be taken to avoid extravasation of phenylephrine hydrochloride.

5.4 Bradycardia

Phenylephrine hydrochloride can cause severe bradycardia and decreased cardiac output.

5.5 Allergic Reactions

Phenylephrine hydrochloride contains sodium metabisulfite, a sulfite that may cause allergic-type reactions, including anaphylactic symptoms and life-threatening or less severe asthmatic episodes in certain susceptible people. The overall prevalence of sulfite sensitivity in the general population is unknown and probably low. Sulfite sensitivity is seen more frequently in asthmatic than in nonasthmatic people.

5.6 Renal Toxicity

Phenylephrine hydrochloride can increase the need for renal replacement therapy in patients with septic shock. Monitor renal function.

5.7 Risk of Augmented Pressor Affect in Patients with Autonomic Dysfunction

The increasing blood pressure response to adrenergic drugs, including phenylephrine hydrochloride, can be increased in patients with autonomic dysfunction, as may occur with spinal cord injuries.

5.8 Pressor Effect with Concomitant Oxytocic Drugs

Oxytocic drugs potentiate the increasing blood pressure effect of sympathomimetic pressor amines including phenylephrine hydrochloride [see Drug Interactions (7.1)] , with the potential for hemorrhagic stroke.

6 ADVERSE REACTIONS

Adverse reactions to phenylephrine hydrochloride are primarily attributable to excessive pharmacologic activity. Adverse reactions reported in published clinical studies, observational trials, and case reports of phenylephrine hydrochloride are listed below by body system. Because these reactions are reported voluntarily from a population of uncertain size, it is not always possible to estimate their frequency reliably or to establish a causal relationship to drug exposure.

Cardiac disorders: Reflex bradycardia, lowered cardiac output, ischemia, hypertension, arrhythmias

Gastrointestinal disorders: Epigastric pain, vomiting, nausea

Nervous system disorders: Headache, blurred vision, neck pain, tremors

Vascular disorders: Hypertensive crisis

Respiratory, Thoracic and Mediastinal Disorders: Dyspnea

Skin and subcutaneous tissue disorders: Pruritis

7 DRUG INTERACTIONS

7.1 Interactions that Augment Pressor Effect

The increasing blood pressure effect of phenylephrine hydrochloride is increased in patients receiving:

- Monoamine oxidase inhibitors (MAOI)
- Oxytocin and oxytocic drugs
- Tricyclic antidepressants
- Angiotensin, aldosterone
- Atropine
- Steroids, such as hydrocortisone
- Norepinephrine transporter inhibitors, such as atomoxetine
- Ergot alkaloids, such as methylergonovine maleate

7.2 Interactions that Antagonize the Pressor Effect

The increasing blood pressure effect of phenylephrine hydrochloride is decreased in patients receiving:

- α-adrenergic antagonists
- Phosphodiesterase Type 5 inhibitors
- Mixed α- and β-receptor antagonists
- Calcium channel blockers, such as nifedipine
- Benzodiazepines
- ACE inhibitors
- Centrally acting sympatholytic agents, such as reserpine, guanfacine.

8 USE IN SPECIFIC POPULATIONS

8.1 Pregnancy

Pregnancy Category C

Risk Summary

There are no adequate or well-controlled studies with phenylephrine hydrochloride injection in pregnant women, nor have animal reproduction studies been conducted. Published studies in normotensive pregnant rabbits report early onset labor, increased fetal lethality, and adverse placental effects with subcutaneous phenylephrine administration during gestation at doses approximately 1.9-times the total daily human dose. Published studies in normotensive pregnant sheep report decreased uterine blood flow and decreased PaO2 in the fetus with intravenous phenylephrine administration during late gestation at doses less than and similar to the human dose. It is not known whether phenylephrine hydrochloride, can cause fetal harm when administered to a pregnant woman. Phenylephrine hydrochloride, should be given to a pregnant woman only if the potential benefit justifies the potential risk to the fetus.

Clinical Considerations

Labor and Delivery

The most common maternal adverse reactions reported in published studies of phenylephrine use during neuraxial anesthesia during Cesarean delivery include nausea and vomiting, bradycardia, reactive hypertension, and transient arrhythmias. Phenylephrine, when administered during labor or delivery, does not appear to alter either neonatal Apgar scores or umbilical artery blood-gas status.

Data

Animal Data

Studies in the published literature evaluating subcutaneously administered phenylephrine (0.33 mg/kg, TID) in normotensive pregnant rabbits reported fetal deaths, adverse histopathology findings in the placenta (necrosis, calcification and thickened vascular walls with narrowed lumen) and possible teratogenic effects (one incidence of clubbed feet, partial development of the intestine) when treatment was initiated during the first trimester or later; and premature labor when treatment was initiated at the second trimester or later. The doses administered were 1.9- times the total daily human dose of 10 mg/day based on a body surface area comparison. Published studies in pregnant normotensive sheep demonstrate that intravenous phenylephrine (4 mcg/kg/min for 30 minutes, equivalent to 3.6 to 4.1 mcg/kg/min human equivalent dose based on body surface area) administered during the third trimester of pregnancy decreased uterine blood flow by 42%. This dose is 1.1- to 1.2-times the human bolus dose of 200 mcg/60 kg person based on body surface area. Mean fetal blood pressure and heart rate fluctuated above and below controls by about 7% during the infusion. Fetal PaO2 was significantly decreased by approximately 26% of control during the infusion. Likewise, PaCO2 was increased and pH was decreased. The clinical significance of these findings is not clear; however, the results suggest the potential for cardiovascular effects on the fetus when phenylephrine is used during pregnancy.

8.3 Nursing Mothers

It is not known whether phenylephrine is present in human milk. The developmental and health benefits of breastfeeding should be considered along with the mother’s clinical need for phenylephrine hydrochloride and any potential adverse effects on the breastfed child from the drug or from the underlying maternal condition. Exercise caution when phenylephrine hydrochloride injection is administered to a nursing woman.

8.4 Pediatric Use

Safety and effectiveness in pediatric patients have not been established.

8.5 Geriatric Use

Clinical studies of phenylephrine did not include sufficient numbers of subjects aged 65 and over to determine whether they respond differently from younger subjects. Other reported clinical experience has not identified differences in responses between the elderly and younger patients. In general, dose selection for an elderly patient should be cautious, usually starting at the low end of the dosing range, reflecting the greater frequency of decreased hepatic, renal, or cardiac function, and of concomitant disease or other drug therapy.

8.6 Hepatic Impairment

In patients with liver cirrhosis [Child Pugh Class B and Class C], dose-response data indicate decreased responsiveness to phenylephrine. Start dosing in the recommended dose range but consider that you may need to give more phenylephrine in this population.

8.7 Renal Impairment

In patients with end stage renal disease (ESRD), dose-response data indicate increased responsiveness to phenylephrine. Consider starting at the lower end of the recommended dose range, and adjusting dose based on the target blood pressure goal.

10 OVERDOSAGE

Overdose of phenylephrine hydrochloride can cause a rapid rise in blood pressure. Symptoms of overdose include headache, vomiting, hypertension, reflex bradycardia, a sensation of fullness in the head, tingling of the extremities, and cardiac arrhythmias including ventricular extrasystoles and ventricular tachycardia.

11 DESCRIPTION

Phenylephrine is an alpha-1 adrenergic receptor agonist. Phenylephrine hydrochloride injection USP, 10 mg/mL is a sterile, nonpyrogenic solution for intravenous use. It must be diluted before administration as an intravenous bolus or continuous intravenous infusion. The chemical name of phenylephrine hydrochloride is (-)- m-hydroxy-α-[(methylamino)methyl]benzyl alcohol hydrochloride, and its structural formula is depicted below:

Phenylephrine hydrochloride, USP is a white or practically white crystals with a molecular formula of C9H13NO2 • HCl and a molecular weight of 203.67. It is freely soluble in water and in alcohol.

Phenylephrine hydrochloride injection USP, 10 mg/mL is sensitive to light.

Each mL contains: phenylephrine hydrochloride, USP 10 mg, sodium chloride 3.5 mg, trisodium citrate dihydrate 4 mg, citric acid monohydrate 1 mg, and sodium metabisulfite 2 mg in water for injection. The pH is adjusted with sodium hydroxide and/or hydrochloric acid if necessary. The pH range is 3.5 to 5.5.

12 CLINICAL PHARMACOLOGY

12.1 Mechanism of Action

Phenylephrine hydrochloride is an α-1 adrenergic receptor agonist.

12.2 Pharmacodynamics

Interaction of phenylephrine with α1-adrenergic receptors on vascular smooth muscle cells causes activation of the cells and results in vasoconstriction. Following phenylephrine hydrochloride intravenous administration, increases in systolic and diastolic blood pressures, mean arterial blood pressure, and total peripheral vascular resistance are observed. The onset of blood pressure increase following an intravenous bolus phenylephrine hydrochloride administration is rapid, typically within minutes. As blood pressure increases following intravenous administration, vagal activity also increases, resulting in reflex bradycardia. Phenylephrine has activity on most vascular beds, including renal, pulmonary, and splanchnic arteries.

12.3 Pharmacokinetics

Following an intravenous infusion of phenylephrine hydrochloride, the observed effective half-life was approximately 5 minutes. The steady-state volume of distribution of approximately 340 L suggests a high distribution into organs and peripheral tissues. The average total serum clearance is approximately 2100 mL/min. The observed phenylephrine plasma terminal elimination half-life was 2.5 hours.

Phenylephrine is metabolized primarily by monoamine oxidase and sulfotransferase. After intravenous administration of radiolabeled phenylephrine, approximately 80% of the total dose was eliminated within first 12 hours; and approximately 86% of the total dose was recovered in the urine within 48 hours. The excreted unchanged parent drug was 16% of the total dose in the urine at 48 hours post intravenous administration. There are two major metabolites, with approximately 57 and 8% of the total dose excreted as m-hydroxymandelic acid and sulfate conjugates, respectively. The metabolites are considered not pharmacologically active.

13 NONCLINICAL TOXICOLOGY

13.1 Carcinogenesis, Mutagenesis, Impairment of Fertility

Carcinogenesis: Long-term animal studies that evaluated the carcinogenic potential of orally administered phenylephrine hydrochloride in F344/N rats and B6C3F1 mice were completed by the National Toxicology Program using the dietary route of administration. There was no evidence of carcinogenicity in mice administered approximately 270 mg/kg/day (131-times the maximum recommended daily dose of < 10 mg/day) or rats administered approximately 50 mg/kg/day (48-times the maximum recommended daily dose of < 10 mg/day) based on body surface area comparisons.

Mutagenesis: Phenylephrine hydrochloride tested negative in the in vitro bacterial reverse mutation assay (S.typhimurium strains TA98, TA100, TA1535 and TA1537), the in vitro chromosomal aberrations assay, the in vitro sister chromatid exchange assay, and the in vivo rat micronucleus assay. Positive results were reported in only one of two replicates of the in vitro mouse lymphoma assay.

Impairment of Fertility: Studies to evaluate the effect of phenylephrine on fertility have not been conducted.

14 CLINICAL STUDIES

The evidence for the efficacy of phenylephrine hydrochloride is derived from studies of phenylephrine hydrochloride in the published literature. The literature support includes 16 studies evaluating the use of intravenous phenylephrine to treat hypotension during anesthesia. The 16 studies include 9 studies where phenylephrine was used in low-risk (ASA 1 and 2) pregnant women undergoing neuraxial anesthesia during Cesarean delivery, 6 studies in non-obstetric surgery under general anesthesia, and 1 study in non-obstetric surgery under combined general and neuraxial anesthesia. Phenylephrine has been shown to raise systolic and mean blood pressure when administered either as a bolus dose or by continuous infusion following the development of hypotension during anesthesia.

16 HOW SUPPLIED/STORAGE AND HANDLING

Phenylephrine Hydrochloride Injection, USP is a sterile, clear, colorless solution and supplied in 1 mL single-dose glass vials. Each mL contains phenylephrine hydrochloride USP, 10 mg.

10 mg/mL (1 mL)

1 mL Single -dose Vial: NDC 70121-1577-1

25 Vials in a Carton: NDC 70121-1577-5

Store phenylephrine hydrochloride injection USP, 10 mg/mL at 20° to 25°C (68° to 77°F); excursions permitted between 15° to 30°C (59° to 86°F) [see USP Controlled Room Temperature].

Protect from light. Store in carton until time of use. Vial stoppers are not manufactured with natural rubber latex.

The diluted solution should not be held for more than 4 hours at room temperature or for more than 24 hours under refrigerated conditions. Discard any unused portion.

17 PATIENT COUNSELING INFORMATION

If applicable, inform patients, family member, or caregiver that certain medical conditions and medications might influence how phenylephrine hydrochloride injection works.

Manufactured by:

Amneal Pharmaceuticals Pvt. Ltd.

Parenteral Unit

Ahmedabad 382213, INDIA

Distributed by:

Amneal Biosciences LLC

Bridgewater, NJ 08807

Rev. 04-2018-00

PRINCIPAL DISPLAY PANEL - VIAL LABEL

Name: Phenylephrine Hydrochloride Injection, USP

Strength: 10 mg/mL (1 mL)

Rx Only

Vial Label

PRINCIPAL DISPLAY PANEL - OUTER PACKAGE

NDC 71872-7159-1

RX ONLY

Phenylephrine Hydrochloride Injection, USP

1 - 10 mg/mL 1 mL Single Dose Vial

For Intravenous Use.

Must be diluted.

Protect from light.